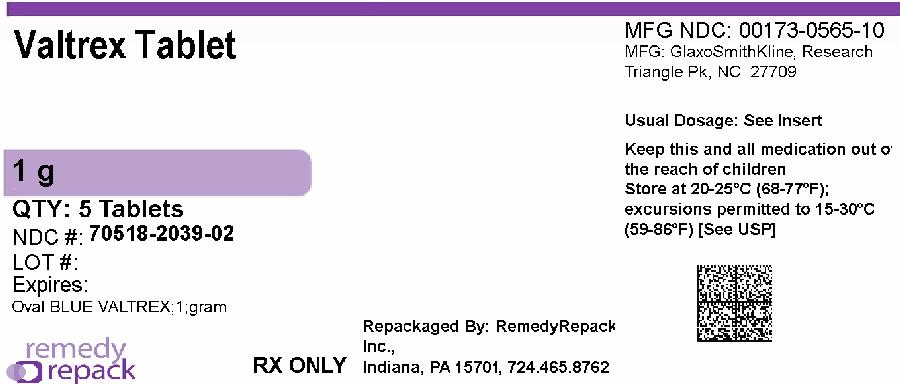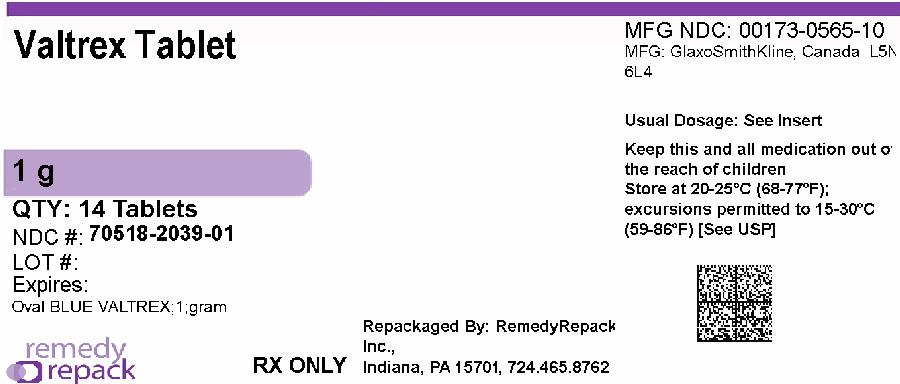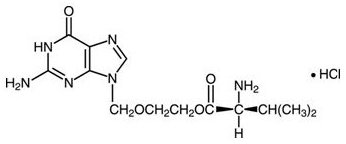 DRUG LABEL: VALTREX
NDC: 70518-2039 | Form: TABLET, FILM COATED
Manufacturer: REMEDYREPACK INC.
Category: prescription | Type: HUMAN PRESCRIPTION DRUG LABEL
Date: 20260130

ACTIVE INGREDIENTS: VALACYCLOVIR HYDROCHLORIDE 1 g/1 1
INACTIVE INGREDIENTS: CARNAUBA WAX; SILICON DIOXIDE; CROSPOVIDONE (120 .MU.M); FD&C BLUE NO. 2; HYPROMELLOSE, UNSPECIFIED; MAGNESIUM STEARATE; MICROCRYSTALLINE CELLULOSE; POLYETHYLENE GLYCOL, UNSPECIFIED; POLYSORBATE 80; POVIDONE, UNSPECIFIED; TITANIUM DIOXIDE

HIGHLIGHTS OF PRESCRIBING INFORMATION

These highlights do not include all the information needed to use VALTREX safely and effectively. See full prescribing information for VALTREX.
VALTREX (valacyclovir) tablets, for oral use
Initial U.S. Approval: 1995

RECENT MAJOR CHANGES

Contraindications (4) | 11/2025
Warnings and Precautions, Severe Cutaneous Adverse Reactions (5.4) | 11/2025

1 INDICATIONS AND USAGE

VALTREX is a deoxynucleoside analogue DNA polymerase inhibitor indicated for:

Adult Patients (1.1)

- Cold Sores (Herpes Labialis)
- Genital Herpes
  - Treatment in immunocompetent patients (initial or recurrent episode)
  - Suppression in immunocompetent or HIV-1−infected patients
  - Reduction of transmission
- Herpes Zoster

Pediatric Patients (1.2)

- Cold Sores (Herpes Labialis)
- Chickenpox

Limitations of Use (1.3)

The efficacy and safety of VALTREX have not been established in immunocompromised patients other than for the suppression of genital herpes in HIV-1−infected patients.

2 DOSAGE AND ADMINISTRATION

Adult Dosage(2.1)
Cold Sores | 2 grams every 12 hours for 1 day
Genital Herpes
Initial episode | 1 gram twice daily for 10 days
Recurrent episodes | 500 mg twice daily for 3 days
Suppressive therapy
Immunocompetent patients | 1 gram once daily
Alternate dose in patients with less than or equal to 9 recurrences/year | 500 mg once daily
HIV-1−infected patients | 500 mg twice daily
Reduction of transmission | 500 mg once daily
Herpes Zoster | 1 gram 3 times daily for 7 days
Pediatric Dosage(2.2)
Cold Sores (aged greater than or equal to 12 years) | 2 grams every 12 hours for 1 day
Chickenpox (aged 2 to less than 18 years) | 20 mg/kg 3 times daily for 5 days; not to exceed 1 gram 3 times daily

Valacyclovir oral suspension (25 mg/mL or 50 mg/mL) can be prepared from the 500 mg VALTREX tablets. (2.3)

3 DOSAGE FORMS AND STRENGTHS

Tablets: 1 gram (partially scored) (3)

4 CONTRAINDICATIONS

Hypersensitivity to valacyclovir (e.g., anaphylaxis), acyclovir, or any component of the formulation. (4)

5 WARNINGS AND PRECAUTIONS

- Thrombotic thrombocytopenic purpura/hemolytic uremic syndrome (TTP/HUS): Has occurred in patients with advanced HIV-1 disease and in allogenic bone marrow transplant and renal transplant patients receiving 8 grams per day of VALTREX in clinical trials. Discontinue treatment if clinical symptoms and laboratory findings consistent with TTP/HUS occur. (5.1)
- Acute renal failure: May occur in elderly patients (with or without reduced renal function), patients with underlying renal disease who receive higher-than-recommended doses of VALTREX for their level of renal function, patients who receive concomitant nephrotoxic drugs, or inadequately hydrated patients. Use with caution in elderly patients and reduce dosage in patients with renal impairment. (2.4, 5.2)
- Central nervous system adverse reactions (e.g., agitation, hallucinations, confusion, and encephalopathy): May occur in both adult and pediatric patients (with or without reduced renal function) and in patients with underlying renal disease who receive higher-than-recommended doses of VALTREX for their level of renal function. Elderly patients are more likely to have central nervous system adverse reactions. Use with caution in elderly patients and reduce dosage in patients with renal impairment. (2.4, 5.3)
- Severe cutaneous adverse reactions (SCARs): Including acute generalized exanthematous pustulosis (AGEP), drug reaction with eosinophilia and systemic symptoms (DRESS), toxic epidermal necrolysis (TEN), and Stevens-Johnson syndrome (SJS) have been reported during the postmarketing experience with valacyclovir. Discontinue VALTREX immediately if a painful rash with mucosal involvement or a progressive severe rash develops, and closely monitor clinical status. (5.4)

6 ADVERSE REACTIONS

- The most common adverse reactions reported in at least one indication by greater than 10% of adult subjects treated with VALTREX and more commonly than in subjects treated with placebo are headache, nausea, and abdominal pain. (6.1)
- The only adverse reaction occurring in greater than 10% of pediatric subjects aged less than 18 years was headache. (6.2)

To report SUSPECTED ADVERSE REACTIONS, contact GlaxoSmithKline at 1-888-825-5249 or FDA at 1-800-FDA-1088 or www.fda.gov/medwatch.

FULL PRESCRIBING INFORMATION

1 INDICATIONS AND USAGE

1.1 Adult Patients

Cold Sores (Herpes Labialis)

VALTREX is indicated for treatment of cold sores (herpes labialis). The efficacy of VALTREX initiated after the development of clinical signs of a cold sore (e.g., papule, vesicle, or ulcer) has not been established.

Genital Herpes

Initial Episode:VALTREX is indicated for treatment of the initial episode of genital herpes in immunocompetent adults. The efficacy of treatment with VALTREX when initiated more than 72 hours after the onset of signs and symptoms has not been established.

Recurrent Episodes:VALTREX is indicated for treatment of recurrent episodes of genital herpes in immunocompetent adults. The efficacy of treatment with VALTREX when initiated more than 24 hours after the onset of signs and symptoms has not been established.

Suppressive Therapy:VALTREX is indicated for chronic suppressive therapy of recurrent episodes of genital herpes in immunocompetent and in HIV-1−infected adults. The efficacy and safety of VALTREX for the suppression of genital herpes beyond 1 year in immunocompetent patients and beyond 6 months in HIV-1−infected patients have not been established.

Reduction of Transmission:VALTREX is indicated for the reduction of transmission of genital herpes in immunocompetent adults. The efficacy of VALTREX for the reduction of transmission of genital herpes beyond 8 months in discordant couples has not been established. The efficacy of VALTREX for the reduction of transmission of genital herpes in individuals with multiple partners and non‑heterosexual couples has not been established. Safer sex practices should be used with suppressive therapy (see current Centers for Disease Control and Prevention [CDC] Sexually Transmitted Diseases Treatment Guidelines).

Herpes Zoster

VALTREX is indicated for the treatment of herpes zoster (shingles) in immunocompetent adults. The efficacy of VALTREX when initiated more than 72 hours after the onset of rash and the efficacy and safety of VALTREX for treatment of disseminated herpes zoster have not been established.

1.2 Pediatric Patients

Cold Sores (Herpes Labialis)

VALTREX is indicated for the treatment of cold sores (herpes labialis) in pediatric patients aged greater than or equal to 12 years. The efficacy of VALTREX initiated after the development of clinical signs of a cold sore (e.g., papule, vesicle, or ulcer) has not been established.

Chickenpox

VALTREX is indicated for the treatment of chickenpox in immunocompetent pediatric patients aged 2 to less than 18 years. Based on efficacy data from clinical trials with oral acyclovir, treatment with VALTREX should be initiated within 24 hours after the onset of rash [see Clinical Studies (14.4)] .

1.3 Limitations of Use

The efficacy and safety of VALTREX have not been established in:

- Immunocompromised patients other than for the suppression of genital herpes in HIV‑1−infected patients with a CD4+ cell count greater than or equal to 100 cells/mm^3.
- Patients aged less than 12 years with cold sores (herpes labialis).
- Patients aged less than 2 years or greater than or equal to 18 years with chickenpox.
- Patients aged less than 18 years with genital herpes.
- Patients aged less than 18 years with herpes zoster.
- Neonates and infants as suppressive therapy following neonatal herpes simplex virus (HSV) infection.

2 DOSAGE AND ADMINISTRATION

- VALTREX may be given without regard to meals.
- Valacyclovir oral suspension (25 mg/mL or 50 mg/mL) may be prepared extemporaneously from 500-mg VALTREX tablets for use in pediatric patients for whom a solid dosage form is not appropriate [see Dosage and Administration (2.3)] .

2.1 Adult Dosing Recommendations

Cold Sores (Herpes Labialis)

The recommended dosage of VALTREX for treatment of cold sores is 2 grams twice daily for 1 day taken 12 hours apart. Therapy should be initiated at the earliest symptom of a cold sore (e.g., tingling, itching, or burning).

Genital Herpes

Initial Episode:The recommended dosage of VALTREX for treatment of initial genital herpes is 1 gram twice daily for 10 days. Therapy was most effective when administered within 48 hours of the onset of signs and symptoms.

Recurrent Episodes:The recommended dosage of VALTREX for treatment of recurrent genital herpes is 500 mg twice daily for 3 days. Initiate treatment at the first sign or symptom of an episode.

Suppressive Therapy:The recommended dosage of VALTREX for chronic suppressive therapy of recurrent genital herpes is 1 gram once daily in patients with normal immune function. In patients with a history of 9 or fewer recurrences per year, an alternative dose is 500 mg once daily.

In HIV‑1−infected patients with a CD4+ cell count greater than or equal to 100 cells/mm^3, the recommended dosage of VALTREX for chronic suppressive therapy of recurrent genital herpes is 500 mg twice daily.

Reduction of Transmission:The recommended dosage of VALTREX for reduction of transmission of genital herpes in patients with a history of 9 or fewer recurrences per year is 500 mg once daily for the source partner.

Herpes Zoster

The recommended dosage of VALTREX for treatment of herpes zoster is 1 gram 3 times daily for 7 days. Therapy should be initiated at the earliest sign or symptom of herpes zoster and is most effective when started within 48 hours of the onset of rash.

2.2 Pediatric Dosing Recommendations

Cold Sores (Herpes Labialis)

The recommended dosage of VALTREX for the treatment of cold sores in pediatric patients aged greater than or equal to 12 years is 2 grams twice daily for 1 day taken 12 hours apart. Therapy should be initiated at the earliest symptom of a cold sore (e.g., tingling, itching, or burning).

Chickenpox

The recommended dosage of VALTREX for treatment of chickenpox in immunocompetent pediatric patients aged 2 to less than 18 years is 20 mg/kg administered 3 times daily for 5 days. The total dose should not exceed 1 gram 3 times daily. Therapy should be initiated at the earliest sign or symptom [see Use in Specific Populations (8.4), Clinical Pharmacology (12.3), Clinical Studies (14.4)] .

2.3 Extemporaneous Preparation of Oral Suspension

Ingredients and Preparation per USP‑ NF

VALTREX tablets 500 mg, cherry flavor, and Suspension Structured Vehicle USP-NF (SSV). Valacyclovir oral suspension (25 mg/mL or 50 mg/mL) should be prepared in lots of 100 mL.

Instructions for Preparing Suspension at Time of Dispensing

- Prepare SSV according to the USP-NF.
- Using a pestle and mortar, grind the required number of VALTREX 500-mg tablets until a fine powder is produced (5 VALTREX tablets for 25-mg/mL suspension; 10 VALTREX tablets for 50-mg/mL suspension).
- Gradually add approximately 5-mL aliquots of SSV to the mortar and triturate the powder until a paste has been produced. Ensure that the powder has been adequately wetted.
- Continue to add approximately 5-mL aliquots of SSV to the mortar, mixing thoroughly between additions, until a concentrated suspension is produced, to a minimum total quantity of 20 mL SSV and a maximum total quantity of 40 mL SSV for both the 25-mg/mL and 50-mg/mL suspensions.
- Transfer the mixture to a suitable 100-mL measuring flask.
- Transfer the cherry flavor* to the mortar and dissolve in approximately 5 mL of SSV. Once dissolved, add to the measuring flask.
- Rinse the mortar at least 3 times with approximately 5-mL aliquots of SSV, transferring the rinsing to the measuring flask between additions.
- Make the suspension to volume (100 mL) with SSV and shake thoroughly to mix.
- Transfer the suspension to an amber glass medicine bottle with a child-resistant closure.
- The prepared suspension should be labeled with the following information “Shake well before using. Store suspension between 2°C to 8°C (36°F to 46°F) in a refrigerator. Discard after 28 days.”

*The amount of cherry flavor added is as instructed by the suppliers of the cherry flavor.

2.4 Patients with Renal Impairment

Dosage recommendations for adult patients with reduced renal function are provided in Table 1 [see Use in Specific Populations (8.5, 8.6), Clinical Pharmacology (12.3)] . Data are not available for the use of VALTREX in pediatric patients with a creatinine clearance less than 50 mL/min/1.73 m^2.

Table 1. VALTREX Dosage Recommendations for Adults with Renal Impairment
Indications | Normal Dosage; Regimen; (Creatinine Clearance ≥50 mL/min) | Creatinine Clearance (mL/min)
Indications | Normal Dosage; Regimen; (Creatinine Clearance ≥50 mL/min) | 30-49 | 10-29 | <10
Cold sores (Herpes Labialis); Do not exceed 1 day of treatment. | Two 2-gram doses taken 12 hours apart | Two 1-gram doses taken 12 hours apart | Two 500-mg doses taken 12 hours apart | 500-mg single dose
Genital herpes:; Initial episode | 1 gram every 12 hours | no reduction | 1 gram every 24 hours | 500 mg every 24 hours
Genital herpes:; Recurrent episode | 500 mg every 12 hours | no reduction | 500 mg every 24 hours | 500 mg every 24 hours
Genital herpes:; Suppressive therapy
Immunocompetent patients | 1 gram every 24 hours | no reduction | 500 mg every 24 hours | 500 mg every 24 hours
Alternate dose for immunocompetent patients with less than or equal to 9 recurrences/year | 500 mg every 24 hours | no reduction | 500 mg every 48 hours | 500 mg every 48 hours
HIV‑1−infected patients | 500 mg every 12 hours | no reduction | 500 mg every 24 hours | 500 mg every 24 hours
Herpes zoster | 1 gram every 8 hours | 1 gram every 12 hours | 1 gram every 24 hours | 500 mg every 24 hours

Hemodialysis

Patients requiring hemodialysis should receive the recommended dose of VALTREX after hemodialysis. During hemodialysis, the half-life of acyclovir after administration of VALTREX is approximately 4 hours. About one-third of acyclovir in the body is removed by dialysis during a 4-hour hemodialysis session.

Peritoneal Dialysis

There is no information specific to administration of VALTREX in patients receiving peritoneal dialysis. The effect of chronic ambulatory peritoneal dialysis (CAPD) and continuous arteriovenous hemofiltration/dialysis (CAVHD) on acyclovir pharmacokinetics has been studied. The removal of acyclovir after CAPD and CAVHD is less pronounced than with hemodialysis, and the pharmacokinetic parameters closely resemble those observed in patients with end-stage renal disease (ESRD) not receiving hemodialysis. Therefore, supplemental doses of VALTREX should not be required following CAPD or CAVHD.

3 DOSAGE FORMS AND STRENGTHS

Tablets:

- 1-gram: Each blue, film‑coated, capsule‑shaped tablet, with a partial scorebar on both sides, printed with “VALTREX 1 gram” contains 1.112 grams of valacyclovir hydrochloride equivalent to 1 gram of the free base.

4 CONTRAINDICATIONS

VALTREX is contraindicated in patients who have had a demonstrated clinically significant hypersensitivity reaction [e.g., anaphylaxis, severe cutaneous adverse reactions (SCARs)] to valacyclovir, acyclovir, or any component of the formulation [see Warnings and Precautions (5.4), Adverse Reactions (6.3)] .

5 WARNINGS AND PRECAUTIONS

5.1 Thrombotic Thrombocytopenic Purpura/Hemolytic Uremic Syndrome (TTP/HUS)

TTP/HUS, in some cases resulting in death, has occurred in patients with advanced HIV-1 disease and also in allogeneic bone marrow transplant and renal transplant recipients participating in clinical trials of VALTREX at doses of 8 grams per day. Treatment with VALTREX should be stopped immediately if clinical signs, symptoms, and laboratory abnormalities consistent with TTP/HUS occur.

5.2 Acute Renal Failure

Cases of acute renal failure have been reported in:

- Elderly patients with or without reduced renal function. Caution should be exercised when administering VALTREX to geriatric patients, and dosage reduction is recommended for those with impaired renal function [see Dosage and Administration (2.4), Use in Specific Populations (8.5)].
- Patients with underlying renal disease who received higher-than-recommended doses of VALTREX for their level of renal function. Dosage reduction is recommended when administering VALTREX to patients with renal impairment [see Dosage and Administration (2.4), Use in Specific Populations (8.6)].
- Patients receiving other nephrotoxic drugs. Caution should be exercised when administering VALTREX to patients receiving potentially nephrotoxic drugs.
- Patients without adequate hydration. Precipitation of acyclovir in renal tubules may occur when the solubility (2.5 mg/mL) is exceeded in the intratubular fluid. Adequate hydration should be maintained for all patients.

In the event of acute renal failure and anuria, the patient may benefit from hemodialysis until renal function is restored [see Dosage and Administration (2.4), Adverse Reactions (6.3)] .

5.3 Central Nervous System Effects

Central nervous system adverse reactions, including agitation, hallucinations, confusion, delirium, seizures, and encephalopathy, have been reported in both adult and pediatric patients with or without reduced renal function and in patients with underlying renal disease who received higher-than-recommended doses of VALTREX for their level of renal function. Elderly patients are more likely to have central nervous system adverse reactions. VALTREX should be discontinued if central nervous system adverse reactions occur [see Adverse Reactions (6.3), Use in Specific Populations (8.5, 8.6)].

5.4 Severe Cutaneous Adverse Reactions

Severe cutaneous adverse reactions (SCARs), including acute generalized exanthematous pustulosis (AGEP), drug reaction with eosinophilia and systemic symptoms (DRESS), Stevens‑Johnson syndrome (SJS), and toxic epidermal necrolysis (TEN) have been reported during postmarketing experience with valacyclovir [see Contraindications (4) and Adverse Reactions (6.3)] . Discontinue VALTREX immediately if a painful rash with mucosal involvement or a progressive severe rash develops. Closely monitor clinical status and initiate appropriate therapy. VALTREX is contraindicated in patients who have developed SCARs with the use of valacyclovir or acyclovir, or any component of the formulation [see Contraindications (4), Adverse Reactions (6.3)].

6 ADVERSE REACTIONS

The following serious adverse reactions are discussed in greater detail in other sections of the labeling:

- Thrombotic Thrombocytopenic Purpura/Hemolytic Uremic Syndrome [see Warnings and Precautions (5.1)].
- Acute Renal Failure [see Warnings and Precautions (5.2)] .
- Central Nervous System Effects [see Warnings and Precautions (5.3)] .
- Severe Cutaneous Adverse Reactions [see Warnings and Precautions (5.4)] .

The most common adverse reactions reported in at least 1 indication by greater than 10% of adult subjects treated with VALTREX and observed more frequently with VALTREX compared with placebo are headache, nausea, and abdominal pain. The only adverse reaction reported in greater than 10% of pediatric subjects aged less than 18 years was headache.

6.1 Clinical Trials Experience in Adult Subjects

Because clinical trials are conducted under widely varying conditions, adverse reaction rates observed in the clinical trials of a drug cannot be directly compared with rates in the clinical trials of another drug and may not reflect the rates observed in practice.

Cold Sores (Herpes Labialis)

In clinical trials for the treatment of cold sores, the adverse reactions reported by subjects receiving VALTREX 2 grams twice daily (n = 609) or placebo (n = 609) for 1 day, respectively, included headache (14%, 10%) and dizziness (2%, 1%). The frequencies of abnormal ALT (greater than 2 x ULN) were 1.8% for subjects receiving VALTREX compared with 0.8% for placebo. Other laboratory abnormalities (hemoglobin, white blood cells, alkaline phosphatase, and serum creatinine) occurred with similar frequencies in the 2 groups.

Genital Herpes

Initial Episode:In a clinical trial for the treatment of initial episodes of genital herpes, the adverse reactions reported by greater than or equal to 5% of subjects receiving VALTREX 1 gram twice daily for 10 days (n = 318) or oral acyclovir 200 mg 5 times daily for 10 days (n = 318), respectively, included headache (13%, 10%) and nausea (6%, 6%). For the incidence of laboratory abnormalities see Table 2.

Recurrent Episodes:In 3 clinical trials for the episodic treatment of recurrent genital herpes, the adverse reactions reported by greater than or equal to 5% of subjects receiving VALTREX 500 mg twice daily for 3 days (n = 402), VALTREX 500 mg twice daily for 5 days (n = 1,136), or placebo (n = 259), respectively, included headache (16%, 11%, 14%) and nausea (5%, 4%, 5%). For the incidence of laboratory abnormalities see Table 2.

Suppressive Therapy: Suppression of Recurrent Genital Herpes in Immunocompetent Adults:In a clinical trial for the suppression of recurrent genital herpes infections, the adverse reactions reported by subjects receiving VALTREX 1 gram once daily (n = 269), VALTREX 500 mg once daily (n = 266), or placebo (n = 134), respectively, included headache (35%, 38%, 34%), nausea (11%, 11%, 8%), abdominal pain (11%, 9%, 6%), dysmenorrhea (8%, 5%, 4%), depression (7%, 5%, 5%), arthralgia (6%, 5%, 4%), vomiting (3%, 3%, 2%), and dizziness (4%, 2%, 1%). For the incidence of laboratory abnormalities see Table 2.

Suppression of Recurrent Genital Herpes in HIV-1–Infected Subjects:In HIV-1 –infected subjects, frequently reported adverse reactions for VALTREX (500 mg twice daily; n = 194, median days on therapy = 172) and placebo (n = 99, median days on therapy = 59), respectively, included headache (13%, 8%), fatigue (8%, 5%), and rash (8%, 1%). Post-randomization laboratory abnormalities that were reported more frequently in valacyclovir subjects versus placebo included elevated alkaline phosphatase (4%, 2%), elevated ALT (14%, 10%), elevated AST (16%, 11%), decreased neutrophil counts (18%, 10%), and decreased platelet counts (3%, 0%), respectively.

Reduction of Transmission:In a clinical trial for the reduction of transmission of genital herpes, the adverse reactions reported by subjects receiving VALTREX 500 mg once daily (n = 743) or placebo once daily (n = 741), respectively, included headache (29%, 26%), nasopharyngitis (16%, 15%), and upper respiratory tract infection (9%, 10%).

Herpes Zoster

In 2 clinical trials for the treatment of herpes zoster, the adverse reactions reported by subjects receiving VALTREX 1 gram 3 times daily for 7 to 14 days (n = 967) or placebo (n = 195), respectively, included nausea (15%, 8%), headache (14%, 12%), vomiting (6%, 3%), dizziness (3%, 2%), and abdominal pain (3%, 2%). For the incidence of laboratory abnormalities see Table 2.

Table 2. Incidence (%) of Laboratory Abnormalities in Herpes Zoster and Genital Herpes Trial Populations
Laboratory Abnormality | Herpes Zoster |  | Genital Herpes Treatment |  |  | Genital Herpes Suppression
Laboratory Abnormality | VALTREX; 1 gram; 3 Times Daily; (n = 967) | Placebo; (n = 195) | VALTREX; 1 gram Twice Daily; (n = 1,194) | VALTREX; 500 mg Twice Daily; (n = 1,159) | Placebo; (n = 439) | VALTREX; 1 gram Once Daily; (n = 269) | VALTREX; 500 mg Once Daily; (n = 266) | Placebo; (n = 134)
Hemoglobin; (<0.8 x LLN) | 0.8% | 0% | 0.3% | 0.2% | 0% | 0% | 0.8% | 0.8%
White blood cells; (<0.75 x LLN) | 1.3% | 0.6% | 0.7% | 0.6% | 0.2% | 0.7% | 0.8% | 1.5%
Platelet count; (<100,000/mm^3) | 1.0% | 1.2% | 0.3% | 0.1% | 0.7% | 0.4% | 1.1% | 1.5%
AST (SGOT); (>2 x ULN) | 1.0% | 0% | 1.0% | a | 0.5% | 4.1% | 3.8% | 3.0%
Serum creatinine; (>1.5 x ULN) | 0.2% | 0% | 0.7% | 0% | 0% | 0% | 0% | 0%
a Data were not collected prospectively.
LLN = Lower limit of normal.
ULN = Upper limit of normal.

6.2 Clinical Trials Experience in Pediatric Subjects

The safety profile of VALTREX has been studied in 177 pediatric subjects aged 1 month to less than 18 years. Sixty-five of these pediatric subjects, aged 12 to less than 18 years, received oral tablets for 1 to 2 days for treatment of cold sores. The remaining 112 pediatric subjects, aged 1 month to less than 12 years, participated in 3 pharmacokinetic and safety trials and received valacyclovir oral suspension. Fifty-one of these 112 pediatric subjects received oral suspension for 3 to 6 days. The frequency, intensity, and nature of clinical adverse reactions and laboratory abnormalities were similar to those seen in adults.

Pediatric Subjects Aged 12 to Less than 18 Years (Cold Sores)

In clinical trials for the treatment of cold sores, the adverse reactions reported by adolescent subjects receiving VALTREX 2 grams twice daily for 1 day, or VALTREX 2 grams twice daily for 1 day followed by 1 gram twice daily for 1 day (n = 65, across both dosing groups), or placebo (n = 30), respectively, included headache (17%, 3%) and nausea (8%, 0%).

Pediatric Subjects Aged 1 Month to Less than 12 Years

Adverse events reported in more than 1 subject across the 3 pharmacokinetic and safety trials in children aged 1 month to less than 12 years were diarrhea (5%), pyrexia (4%), dehydration (2%), herpes simplex (2%), and rhinorrhea (2%). No clinically meaningful changes in laboratory values were observed.

6.3 Postmarketing Experience

In addition to adverse events reported from clinical trials, the following events have been identified during postmarketing use of VALTREX. Because they are reported voluntarily from a population of unknown size, estimates of frequency cannot be made. These events have been chosen for inclusion due to a combination of their seriousness, frequency of reporting, or potential causal connection to VALTREX.

General

Facial edema, hypertension, tachycardia.

Allergic

Acute hypersensitivity reactions including anaphylaxis, angioedema, dyspnea, pruritus, rash, and urticaria [see Contraindications (4)] .

Central Nervous System (CNS) Symptoms

Aggressive behavior; agitation; ataxia; coma; confusion; decreased consciousness; dysarthria; encephalopathy; mania; and psychosis, including auditory and visual hallucinations, seizures, tremors [see Warnings and Precautions (5.3), Use in Specific Populations (8.5, 8.6)] .

Eye

Visual abnormalities.

Gastrointestinal

Diarrhea.

Hepatobiliary Tract and Pancreas

Liver enzyme abnormalities, hepatitis.

Renal

Renal failure, renal pain (may be associated with renal failure) [see Warnings and Precautions (5.2), Use in Specific Populations (8.5, 8.6)] .

Hematologic

Thrombocytopenia, aplastic anemia, leukocytoclastic vasculitis, TTP/HUS [see Warnings and Precautions (5.1)] .

Skin and Subcutaneous Tissue Disorders

Acute generalized exanthematous pustulosis (AGEP), drug reaction with eosinophilia and systemic symptoms (DRESS), toxic epidermal necrolysis (TEN), Stevens‑Johnson syndrome (SJS), erythema multiforme (EM), rashes including photosensitivity, alopecia [see Contraindications (4), Warnings and Precautions (5.4)] .

7 DRUG INTERACTIONS

No clinically significant drug-drug or drug-food interactions with VALTREX are known [see Clinical Pharmacology (12.3)].

8 USE IN SPECIFIC POPULATIONS

8.1 Pregnancy

Risk Summary

Clinical data over several decades with valacyclovir and its metabolite, acyclovir, in pregnant women, have not identified a drug associated risk of major birth defects. There are insufficient data on the use of valacyclovir regarding miscarriage or adverse maternal or fetal outcomes (see Data). There are risks to the fetus associated with untreated herpes simplex during pregnancy (see Clinical Considerations).

In animal reproduction studies, no evidence of adverse developmental outcomes was observed with valacyclovir when administered to pregnant rats and rabbits at system exposures (AUC) 4 (rats) and 7 (rabbits) times the human exposure at the maximum recommended human dose (MRHD) (see Data).

The estimated background risk of major birth defects and miscarriage for the indicated populations is unknown. All pregnancies have a background risk of birth defect, loss, or other adverse outcomes. In the U.S. general population, the estimated background risk of major birth defects and miscarriage in clinically recognized pregnancies is 2% to 4% and 15% to 20%, respectively.

Clinical Considerations

Disease-Associated Maternal and/or Embryo/Fetal Risk:The risk of neonatal HSV infection varies from 30% to 50% for genital HSV acquired in late pregnancy (third trimester), whereas with HSV acquisition in early pregnancy, the risk of neonatal infection is about 1%. A primary herpes occurrence during the first trimester of pregnancy has been associated with neonatal chorioretinitis, microcephaly, and, in rare cases, skin lesions. In very rare cases, transplacental transmission can occur resulting in congenital infection, including microcephaly, hepatosplenomegaly, intrauterine growth restriction, and stillbirth. Co-infection with HSV increases the risk of perinatal HIV transmission in women who had a clinical diagnosis of genital herpes during pregnancy.

Data

Human Data: Clinical data over several decades with valacyclovir and its metabolite, acyclovir, in pregnant women, based on published literature, have not identified a drug-associated risk of major birth defects. There are insufficient data on the use of valacyclovir regarding miscarriage or adverse maternal or fetal outcomes.

The Acyclovir and the Valacyclovir Pregnancy Registries, both population-based international prospective studies, collected pregnancy data through April 1999. The Acyclovir Registry documented outcomes of 1,246 infants and fetuses exposed to acyclovir during pregnancy (756 with earliest exposure during the first trimester, 197 during the second trimester, 291 during the third trimester, and 2 unknown). The occurrence of major birth defects during first-trimester exposure to acyclovir was 3.2% (95% CI: 2.0% to 5.0%) and during any trimester of exposure was 2.6% (95% CI: 1.8% to 3.8%). The Valacyclovir Pregnancy Registry documented outcomes of 111 infants and fetuses exposed to valacyclovir during pregnancy (28 with earliest exposure in the first trimester, 31 during the second trimester, and 52 during the third trimester).The occurrence of major birth defects during first-trimester exposure to valacyclovir was 4.5% (95% CI: 0.24% to 24.9%) and during any trimester of exposure was 3.9% (95% CI: 1.3% to 10.7%).

Available studies have methodological limitations including insufficient sample size to support conclusions about overall malformation risk or for making comparisons of the frequencies of specific birth defects.

Animal Data: Valacyclovir was administered orally to pregnant rats and rabbits (up to 400 mg/kg/day) during organogenesis (Gestation Days 6 through 15, and 6 through 18, respectively). No adverse embryo-fetal effects were observed in rats and rabbits at acyclovir exposures (AUC) of up to approximately 4 (rats) and 7 (rabbits) times the exposure in humans at the MRHD. Early embryo death, fetal growth retardation (weight and length), and variations in fetal skeletal development (primarily extra ribs and delayed ossification of sternebrae) were observed in rats and associated with maternal toxicity (200 mg/kg/day; approximately 6 times higher than human exposure at the MRHD).

In a pre/postnatal development study, valacyclovir was administered orally to pregnant rats (up to 200 mg/kg/day from Gestation Day 15 to Post-Partum Day 20) from late gestation through lactation. No significant adverse effects were observed in offspring exposed daily from before birth through lactation at maternal exposures (AUC) of approximately 6 times higher than human exposures at the MRHD.

8.2 Lactation

Risk Summary

Although there is no information on the presence of valacyclovir in human milk, its metabolite, acyclovir, is present in human milk following oral administration of valacyclovir. Based on published data, a 500-mg maternal dose of VALTREX twice daily would provide a breastfed child with an oral acyclovir dosage of approximately 0.6 mg/kg/day (see Data). There is no data on the effects of valacyclovir or acyclovir on the breastfed child or on milk production. The developmental and health benefits of breastfeeding should be considered along with the mother’s clinical need for VALTREX and any potential adverse effects on the breastfed child from VALTREX or from the underlying maternal condition.

Data

Following oral administration of a 500-mg dose of VALTREX to 5 lactating women, peak acyclovir concentrations (Cmax) in breast milk ranged from 0.5 to 2.3 times (median 1.4) the corresponding maternal acyclovir serum concentrations. The acyclovir breast milk AUC ranged from 1.4 to 2.6 times (median 2.2) maternal serum AUC. A 500-mg maternal dose of VALTREX twice daily would provide a breastfed child with an oral acyclovir dosage of approximately 0.6 mg/kg/day. Unchanged valacyclovir was not detected in maternal serum, breast milk or infant urine.

8.4 Pediatric Use

VALTREX is indicated for treatment of cold sores in pediatric patients aged greater than or equal to 12 years and for treatment of chickenpox in pediatric patients aged 2 to less than 18 years [see Indications and Usage (1.2), Dosage and Administration (2.2)] .

The use of VALTREX for treatment of cold sores is based on 2 double‑blind, placebo‑controlled clinical trials in healthy adults and adolescents (aged greater than or equal to 12 years) with a history of recurrent cold sores [see Clinical Studies (14.1)] .

The use of VALTREX for treatment of chickenpox in pediatric patients aged 2 to less than 18 years is based on single‑dose pharmacokinetic and multiple‑dose safety data from an open‑label trial with valacyclovir and supported by efficacy and safety data from 3 randomized, double‑blind, placebo‑controlled trials evaluating oral acyclovir in pediatric subjects with chickenpox [see Dosage and Administration (2.2), Adverse Reactions (6.2), Clinical Pharmacology (12.3), Clinical Studies (14.4)] .

The efficacy and safety of valacyclovir have not been established in pediatric patients:

- aged less than 12 years with cold sores
- aged less than 18 years with genital herpes
- aged less than 18 years with herpes zoster
- aged less than 2 years with chickenpox
- for suppressive therapy following neonatal HSV infection.

The pharmacokinetic profile and safety of valacyclovir oral suspension in children aged less than 12 years were studied in 3 open‑label trials. No efficacy evaluations were conducted in any of the 3 trials.

Trial 1 was a single‑dose pharmacokinetic, multiple‑dose safety trial in 27 pediatric subjects aged 1 to less than 12 years with clinically suspected varicella‑zoster virus (VZV) infection [see Dosage and Administration (2.2), Adverse Reactions (6.2), Clinical Pharmacology (12.3), Clinical Studies (14.4)] .

Trial 2 was a single‑dose pharmacokinetic and safety trial in pediatric subjects aged 1 month to less than 6 years who had an active herpes virus infection or who were at risk for herpes virus infection. Fifty‑seven subjects were enrolled and received a single dose of 25 mg/kg valacyclovir oral suspension. In infants and children aged 3 months to less than 6 years, this dose provided comparable systemic acyclovir exposures to that from a 1‑gram dose of valacyclovir in adults (historical data). In infants aged 1 month to less than 3 months, mean acyclovir exposures resulting from a 25‑mg/kg dose were higher (Cmax: ↑30%, AUC: ↑60%) than acyclovir exposures following a 1‑gram dose of valacyclovir in adults. Acyclovir is not approved for suppressive therapy in infants and children following neonatal HSV infections; therefore, valacyclovir is not recommended for this indication because efficacy cannot be extrapolated from acyclovir.

Trial 3 was a single‑dose pharmacokinetic, multiple‑dose safety trial in 28 pediatric subjects aged 1 to less than 12 years with clinically suspected HSV infection. None of the subjects enrolled in this trial had genital herpes. Each subject was dosed with valacyclovir oral suspension 10 mg/kg twice daily for 3 to 5 days. Acyclovir systemic exposures in pediatric subjects following valacyclovir oral suspension were compared with historical acyclovir systemic exposures in immunocompetent adults receiving the solid oral dosage form of valacyclovir or acyclovir for the treatment of recurrent genital herpes. The mean projected daily acyclovir systemic exposures in pediatric subjects across all age‑groups (1 to less than 12 years) were lower (Cmax: ↓20%, AUC: ↓33%) compared with the acyclovir systemic exposures in adults receiving valacyclovir 500 mg twice daily but were higher (daily AUC: ↑16%) than systemic exposures in adults receiving acyclovir 200 mg 5 times daily. Insufficient data are available to support valacyclovir for the treatment of recurrent genital herpes in this age‑group because clinical information on recurrent genital herpes in young children is limited; therefore, extrapolating efficacy data from adults to this population is not possible. Moreover, valacyclovir has not been studied in children aged 1 to less than 12 years with recurrent genital herpes.

8.5 Geriatric Use

Of the total number of subjects in clinical trials of VALTREX, 906 were 65 and over, and 352 were 75 and over. In a clinical trial of herpes zoster, the duration of pain after healing (post-herpetic neuralgia) was longer in subjects 65 and older compared with younger adults. Elderly patients are more likely to have reduced renal function and require dose reduction. Elderly patients are also more likely to have renal or CNS adverse events [see Dosage and Administration (2.4), Warnings and Precautions (5.2, 5.3), Clinical Pharmacology (12.3)] .

8.6 Renal Impairment

Dosage reduction is recommended when administering VALTREX to patients with renal impairment [see Dosage and Administration (2.4), Warnings and Precautions (5.2, 5.3)].

10 OVERDOSAGE

Caution should be exercised to prevent inadvertent overdose [see Use in Specific Populations (8.5, 8.6)] . Precipitation of acyclovir in renal tubules may occur when the solubility (2.5 mg/mL) is exceeded in the intratubular fluid. In the event of acute renal failure and anuria, the patient may benefit from hemodialysis until renal function is restored [see Dosage and Administration (2.4)] .

11 DESCRIPTION

VALTREX (valacyclovir hydrochloride) is the hydrochloride salt of the L‑valyl ester of the antiviral drug acyclovir.

VALTREX tablets are for oral administration. Each tablet contains 556.2 mg or 1.112 grams of valacyclovir hydrochloride equivalent to 500 mg or 1 gram of valacyclovir, respectively, and the inactive ingredients carnauba wax, colloidal silicon dioxide, crospovidone, FD&C Blue No. 2 Lake, hypromellose, magnesium stearate, microcrystalline cellulose, polyethylene glycol, polysorbate 80, povidone, and titanium dioxide. The blue, film‑coated tablets are printed with edible white ink.

The chemical name of valacyclovir hydrochloride is L-valine, 2-[(2-amino-1,6-dihydro-6-oxo-9 H-purin-9-yl)methoxy]ethyl ester, monohydrochloride. It has the following structural formula:

Valacyclovir hydrochloride is a white to off-white powder with the molecular formula C13H20N6O4•HCl and a molecular weight of 360.80. The maximum solubility in water at 25°C is 174 mg/mL. The pkas for valacyclovir hydrochloride are 1.90, 7.47, and 9.43.

12 CLINICAL PHARMACOLOGY

12.1 Mechanism of Action

Valacyclovir is an antiviral drug active against α-herpes viruses [see Microbiology (12.4)].

12.3 Pharmacokinetics

The pharmacokinetics of valacyclovir and acyclovir after oral administration of VALTREX have been investigated in 14 volunteer trials involving 283 adults and in 3 trials involving 112 pediatric subjects aged 1 month to less than 12 years.

Pharmacokinetics in Adults

Absorption and Bioavailability:After oral administration, valacyclovir hydrochloride is rapidly absorbed from the gastrointestinal tract and nearly completely converted to acyclovir and L-valine by first-pass intestinal and/or hepatic metabolism.

The absolute bioavailability of acyclovir after administration of VALTREX is 54.5% ± 9.1% as determined following a 1‑gram oral dose of VALTREX and a 350-mg intravenous acyclovir dose to 12 healthy volunteers. Acyclovir bioavailability from the administration of VALTREX is not altered by administration with food (30 minutes after an 873 Kcal breakfast, which included 51 grams of fat).

Acyclovir pharmacokinetic parameter estimates following administration of VALTREX to healthy adult volunteers are presented in Table 3. There was a less than dose-proportional increase in acyclovir maximum concentration (Cmax) and area under the acyclovir concentration-time curve (AUC) after single-dose and multiple-dose administration (4 times daily) of VALTREX from doses between 250 mg to 1 gram.

There is no accumulation of acyclovir after the administration of valacyclovir at the recommended dosage regimens in adults with normal renal function.

Table 3. Mean (±SD) Plasma Acyclovir Pharmacokinetic Parameters Following Administration of VALTREX to Healthy Adult Volunteers
Dose | Single‑ Dose Administration; (N = 8) |  | Multiple‑ Dose Administrationa; (N = 24, 8 per treatment arm)
Dose | Cmax(±SD); (mcg/mL) | AUC (±SD); (h●mcg/mL) | Cmax(±SD); (mcg/mL) | AUC (±SD); (h●mcg/mL)
100 mg | 0.83 (±0.14) | 2.28 (±0.40) | ND | ND
250 mg | 2.15 (±0.50) | 5.76 (±0.60) | 2.11 (±0.33) | 5.66 (±1.09)
500 mg | 3.28 (±0.83) | 11.59 (±1.79) | 3.69 (±0.87) | 9.88 (±2.01)
750 mg | 4.17 (±1.14) | 14.11 (±3.54) | ND | ND
1,000 mg | 5.65 (±2.37) | 19.52 (±6.04) | 4.96 (±0.64) | 15.70 (±2.27)
a Administered 4 times daily for 11 days.
ND = not done.

Distribution:The binding of valacyclovir to human plasma proteins ranges from 13.5% to 17.9%. The binding of acyclovir to human plasma proteins ranges from 9% to 33%.

Metabolism:Valacyclovir is converted to acyclovir and L-valine by first-pass intestinal and/or hepatic metabolism. Acyclovir is converted to a small extent to inactive metabolites by aldehyde oxidase and by alcohol and aldehyde dehydrogenase. Neither valacyclovir nor acyclovir is metabolized by cytochrome P450 enzymes. Plasma concentrations of unconverted valacyclovir are low and transient, generally becoming non-quantifiable by 3 hours after administration. Peak plasma valacyclovir concentrations are generally less than 0.5 mcg/mL at all doses. After single-dose administration of 1 gram of VALTREX, average plasma valacyclovir concentrations observed were 0.5, 0.4, and 0.8 mcg/mL in subjects with hepatic dysfunction, renal insufficiency, and in healthy subjects who received concomitant cimetidine and probenecid, respectively.

Elimination:The pharmacokinetic disposition of acyclovir delivered by valacyclovir is consistent with previous experience from intravenous and oral acyclovir. Following the oral administration of a single 1-gram dose of radiolabeled valacyclovir to 4 healthy subjects, 46% and 47% of administered radioactivity was recovered in urine and feces, respectively, over 96 hours. Acyclovir accounted for 89% of the radioactivity excreted in the urine. Renal clearance of acyclovir following the administration of a single 1-gram dose of VALTREX to 12 healthy subjects was approximately 255 ± 86 mL/min which represents 42% of total acyclovir apparent plasma clearance.

The plasma elimination half‑life of acyclovir typically averaged 2.5 to 3.3 hours in all trials of VALTREX in subjects with normal renal function.

Specific Populations

Patients with Renal Impairment:Reduction in dosage is recommended in patients with renal impairment [see Dosage and Administration (2.4), Use in Specific Populations (8.5, 8.6)].

Following administration of VALTREX to subjects with ESRD, the average acyclovir half‑life is approximately 14 hours. During hemodialysis, the acyclovir half‑life is approximately 4 hours. Approximately one‑third of acyclovir in the body is removed by dialysis during a 4‑hour hemodialysis session. Apparent plasma clearance of acyclovir in subjects on dialysis was 86.3 ± 21.3 mL/min/1.73 m^2compared with 679.16 ± 162.76 mL/min/1.73 m^2in healthy subjects.

Patients with Hepatic Impairment:Administration of VALTREX to subjects with moderate (biopsy‑proven cirrhosis) or severe (with and without ascites and biopsy-proven cirrhosis) liver disease indicated that the rate but not the extent of conversion of valacyclovir to acyclovir is reduced, and the acyclovir half‑life is not affected. Dosage modification is not recommended for patients with cirrhosis.

Patients with HIV-1 Disease:In 9 subjects with HIV-1 disease and CD4+ cell counts less than 150 cells/mm^3who received VALTREX at a dosage of 1 gram 4 times daily for 30 days, the pharmacokinetics of valacyclovir and acyclovir were not different from that observed in healthy subjects.

Geriatric Patients:After single-dose administration of 1 gram of VALTREX in healthy geriatric subjects, the half‑life of acyclovir was 3.11 ± 0.51 hours compared with 2.91 ± 0.63 hours in healthy younger adult subjects. The pharmacokinetics of acyclovir following single- and multiple‑dose oral administration of VALTREX in geriatric subjects varied with renal function. Dose reduction may be required in geriatric patients, depending on the underlying renal status of the patient [see Dosage and Administration (2.4), Use in Specific Populations (8.5, 8.6)] .

Pediatric Patients:Acyclovir pharmacokinetics have been evaluated in a total of 98 pediatric subjects (aged 1 month to less than 12 years) following administration of the first dose of an extemporaneous oral suspension of valacyclovir [see Adverse Reactions (6.2), Use in Specific Populations (8.4)] . Acyclovir pharmacokinetic parameter estimates following a 20‑mg/kg dose are provided in Table 4.

Table 4. Mean (±SD) Plasma Acyclovir Pharmacokinetic Parameter Estimates Following First-Dose Administration of 20 mg/kg Valacyclovir Oral Suspension to Pediatric Subjects vs. 1-Gram Single Dose of VALTREX to Adults
Parameter | Pediatric Subjects; (20 mg/kg Oral Suspension) |  |  | Adults; 1‑ gram Solid Dose of VALTREXa; (n = 15)
Parameter | 1 -<2 year; (n = 6) | 2 -<6 year; (n = 12) | 6 -<12 year; (n = 8) | Adults; 1‑ gram Solid Dose of VALTREXa; (n = 15)
AUC (mcg•h/mL) | 14.4 (±6.26) | 10.1 (±3.35) | 13.1 (±3.43) | 17.2 (±3.10)
Cmax (mcg/mL) | 4.03 (±1.37) | 3.75 (±1.14) | 4.71 (±1.20) | 4.72 (±1.37)
a Historical estimates using pediatric pharmacokinetic sampling schedule.

Drug Interaction Studies

When VALTREX is coadministered with antacids, cimetidine and/or probenecid, digoxin, or thiazide diuretics in patients with normal renal function, the effects are not considered to be of clinical significance (see below). Therefore, when VALTREX is coadministered with these drugs in patients with normal renal function, no dosage adjustment is recommended.

Antacids:The pharmacokinetics of acyclovir after a single dose of VALTREX (1 gram) were unchanged by coadministration of a single dose of antacids (Al^3+or Mg^++).

Cimetidine:Acyclovir Cmaxand AUC following a single dose of VALTREX (1 gram) increased by 8% and 32%, respectively, after a single dose of cimetidine (800 mg).

Cimetidine plus Probenecid:Acyclovir Cmaxand AUC following a single dose of VALTREX (1 gram) increased by 30% and 78%, respectively, after a combination of cimetidine and probenecid, primarily due to a reduction in renal clearance of acyclovir.

Digoxin:The pharmacokinetics of digoxin were not affected by coadministration of VALTREX 1 gram 3 times daily, and the pharmacokinetics of acyclovir after a single dose of VALTREX (1 gram) was unchanged by coadministration of digoxin (2 doses of 0.75 mg).

Probenecid:Acyclovir Cmaxand AUC following a single dose of VALTREX (1 gram) increased by 22% and 49%, respectively, after probenecid (1 gram).

Thiazide Diuretics:The pharmacokinetics of acyclovir after a single dose of VALTREX (1 gram) were unchanged by coadministration of multiple doses of thiazide diuretics.

12.4 Microbiology

Mechanism of Action

Valacyclovir is a deoxynucleoside analogue DNA polymerase inhibitor. Valacyclovir hydrochloride is rapidly converted to acyclovir, which has demonstrated antiviral activity against HSV types 1 (HSV‑1) and 2 (HSV‑2) and VZV both in cell culture and in vivo.

Acyclovir is a synthetic purine deoxynucleoside that is phosphorylated intracellularly by the viral encoded thymidine kinase (TK; pUL23) of HSV or VZV into acyclovir monophosphate, a nucleotide analogue. The monophosphate is further converted into diphosphate by cellular guanylate kinase and into triphosphate by a number of cellular enzymes. In biochemical assays, acyclovir triphosphate inhibits replication of α-herpes viral DNA. This is accomplished in 3 ways: 1) competitive inhibition of viral DNA polymerase, 2) incorporation and termination of the growing viral DNA chain, and 3) inactivation of the viral DNA polymerase. The greater antiviral activity of acyclovir against HSV compared with VZV is due to its more efficient phosphorylation by the viral TK.

Antiviral Activity

The quantitative relationship between the cell culture susceptibility of herpes viruses to antivirals and the clinical response to therapy has not been established in humans, and virus sensitivity testing has not been standardized. Sensitivity testing results, expressed as the concentration of drug required to inhibit by 50% the growth of virus in cell culture (EC50), vary greatly depending upon a number of factors. Using plaque‑reduction assays, the EC50values against herpes simplex virus isolates range from 0.09 to 60 microM (0.02 to 13.5 mcg/mL) for HSV‑1 and from 0.04 to 44 microM (0.01 to 9.9 mcg/mL) for HSV‑2. The EC50values for acyclovir against most laboratory strains and clinical isolates of VZV range from 0.53 to 48 microM (0.12 to 10.8 mcg/mL). Acyclovir also demonstrates activity against the Oka vaccine strain of VZV with a mean EC50value of 6 microM (1.35 mcg/mL).

Resistance

In Cell Culture:Acyclovir-resistant HSV-1, HSV-2, and VZV strains were isolated in cell culture. Acyclovir-resistant HSV and VZV resulted from mutations in the viral thymidine kinase (TK, pUL23) and DNA polymerase (POL; pUL30) genes. Frameshifts were commonly isolated and result in premature truncation of the HSV TK product with consequent decreased susceptibility to acyclovir. Mutations in the viral TK gene may lead to complete loss of TK activity (TK negative), reduced levels of TK activity (TK partial), or alteration in the ability of viral TK to phosphorylate the drug without an equivalent loss in the ability to phosphorylate thymidine (TK altered). In cell culture, acyclovir resistance-associated substitutions in TK of HSV-1 and HSV-2 were observed (Table 5).

Table 5. Summary of Acyclovir Resistance-Associated Amino Acid Substitutions in Cell Culture
Virus | Gene | Substitution
HSV-1 | TK | P5A, H7Q, L50V, G56V, G59R/V/W/A, G61A/V, K62I/N, T63A, E83K, P84L/S, R89W, D116N, P131S, P155R, F161I/C, R163H/P, A167V, P173L, R176Q/W, Q185R, A189L/V, G200S, G206R, R216S, R220H, L227F, Y239S, T245M, Q261stop, R281stop, T287M, M322K, C336Y, V348A
HSV-2 | TK | L69P, C172R, A175V, T288M
HSV-1 | POL | D368A, Y557S, E597D, V621S, L702H, A719V, S742N, N815S, V817M, Y818C, G841C/S
HSV-2 | POL | No substitutions detected

HSV-Infected Patients:Clinical HSV-1 and HSV-2 isolates obtained from patients who failed treatment for their α-herpes virus infections were evaluated for genotypic changes in the TK and POL genes and for phenotypic resistance to acyclovir (Table 6). HSV isolates with frameshift mutations and resistance-associated substitutions in TK and POL were identified. The listing of substitutions in the HSV TK and POL leading to decreased susceptibility to acyclovir is not all inclusive and additional changes will likely be identified in HSV variants isolated from patients who fail acyclovir-containing regimens. The possibility of viral resistance to acyclovir should be considered in patients who fail to respond or experience recurrent viral shedding during therapy.

Table 6. Summary of Acyclovir Resistance-Associated Amino Acid Substitutions Observed in Treated Patients
Virus | Gene | Substitution
HSV-1 | TK | G6C, R32H, R41H, R51W, Y53C/D/H, Y53stop, D55N, G56D/E/S, P57H, G58N/R, G59R, G61A/E/W, K62N, T63I, Q67stop, S74stop, Y80N, E83K, P84L, Y87H, E95stop, T103P, Q104H, Q104stop, H105P, M121K/L/R, Q125N, M128L, G129D, I143V, A156V, D162A/H/N, R163G/H, L170P, Y172C, P173L/R, A174P, A175V, R176Q/W, R176stop, L178R, S181N, A186P, V187M, A189V, V192A, G200C/D/S, T201P, T202A, V204G, A207P, L208F/H, R216C/H, R220C/H, R221C/H, R222C/H, E226K, D229H, L242P, T245M/P, L249P, Q250stop, C251G, E257K, Q261R, A265T, R281stop, T287M, L288stop, L291R, L297S, L315S, L327R, C336Y, C336stop, Q342stop, T354P, L364P, A365T
HSV-2 | TK | G25A, R34C, G39E, R51W, Y53N/D, G59P, G61A/E/W, S66P, A72S, D78N, P85S, R86P, A94V, L98stop, N100H, I101S, Q103stop, Q105P, A125T, T131P, Y133F, D137stop, F140L, L158P, S169P, R177W, S182N, M183Istop, V192M, G201D, R217H, R221C/H, Q222stop, R223H, D229stop, Y239stop, D231N, L263stop, R271V, P272S, D273R, T287M, C337Y
HSV-1 | POL | K532T, S559L, Q570R, L583V, A605V, V621S, A657T, D672N, V715G, A719T/V, S724N, F733C, E771Q, S775N, L778M, E798K, V813M, N815S, G841S, R842S, I890M, V958L, H1228D
HSV-2 | POL | E250Q, D307N, K533E, A606V, C625R, R628C, E678G, A724V, S725G, S729N, I731F, Q732R, D785N, M789K/T, V818A, N820S, Y823C, Q829R, T843A, M910T, D912N/V, A915V, F923L, T934A, R964H
Note: Many additional pathways to acyclovir resistance likely exist.

Cross-Resistance

Cross-resistance has been observed among HSV isolates carrying frameshift mutations and resistance-associated substitutions, which confer reduced susceptibility to penciclovir (PCV), famciclovir (FCV), and foscarnet (FOS) (Table 7).

Table 7. Summary of Acyclovir Resistance-Associated Amino Acid Substitutions Conferring Cross-Resistance to PCV, FCV or FOS
Cross-Resistant Drug | Virus/Gene | Substitution
PCV/FCV | HSV-1 TK | G6C, R32H, R51W, Y53C/H/N, H58N, G61A, S74stop, E83K, P84L, T103P, Q104stop, D116N, M121R, I143V, P155R, R163G/H, A167V, L170P, Y172C, P173L, A174P, R176Q/W, Q185R, A186P, A189L/V, G200D/S, G206R, L208H, R216C, R220H, R222C/H, Y239S, T245M, Q250stop, Q261stop, R281stop, T287M, L315S, M322K, C336Y, V348A
PCV/FCV | HSV-1 POL | A657T, D672N, V715G, A719V, S724N, E798K, N815S, G841C/S
PCV/FCV | HSV-2 TK | G39E, R51W, Y53N, R86P, Y133F, R177W, R221H, T288M
PCV/FCV | HSV-2 POL | K533E, A606V, C625R, R628C, S729N, Q732R, M789K/T, V818A, N820S, F923L, T934A
FOS | HSV-1 POL | D368A, A605V, D672N, L702H, V715G, A719T/V, S724N, L778M, E798K, V813M, N815S, V817M, G841C/S, I890M
FOS | HSV-2 POL | K533E, A606V, C625R, R628C, A724V, S725G, S729N, I731F, Q732R, M789K/T, V818A, Y823C, D912V, F923L, T934A, R964H

13 NONCLINICAL TOXICOLOGY

13.1 Carcinogenesis, Mutagenesis, Impairment of Fertility

The data presented below include references to the steady‑state acyclovir AUC observed in humans treated with 1 gram of VALTREX given orally 3 times a day to treat herpes zoster. Plasma drug concentrations in animal studies are expressed as multiples of human exposure to acyclovir [see Clinical Pharmacology (12.3)] .

Carcinogenesis

Valacyclovir was noncarcinogenic in lifetime carcinogenicity bioassays at single daily doses (gavage) of valacyclovir giving plasma acyclovir concentrations equivalent to human levels in the mouse bioassay and 1.4 to 2.3 times human levels in the rat bioassay. There was no significant difference in the incidence of tumors between treated and control animals, nor did valacyclovir shorten the latency of tumors.

Mutagenesis

Valacyclovir was tested in 5 genetic toxicity assays. An Ames assay was negative in the absence or presence of metabolic activation. Also negative were an in vitro cytogenetic study with human lymphocytes and a rat cytogenetic study.

In the mouse lymphoma assay, valacyclovir was not mutagenic in the absence of metabolic activation. In the presence of metabolic activation (76% to 88% conversion to acyclovir), valacyclovir was mutagenic.

Valacyclovir was mutagenic in a mouse micronucleus assay.

Impairment of Fertility

Valacyclovir did not impair fertility or reproduction in male or female rats at acyclovir exposures (AUC) 6 times higher than in humans given the MRHD. Testicular atrophy occurred in male rats (orally dosed for 97 days at 18 times the MRHD) and was reversible.

14 CLINICAL STUDIES

14.1 Cold Sores (Herpes Labialis)

Two double‑blind, placebo‑controlled clinical trials were conducted in 1,856 healthy adults and adolescents (aged greater than or equal to 12 years) with a history of recurrent cold sores. Subjects self‑initiated therapy at the earliest symptoms and prior to any signs of a cold sore. The majority of subjects initiated treatment within 2 hours of onset of symptoms. Subjects were randomized to VALTREX 2 grams twice daily on Day 1 followed by placebo on Day 2, VALTREX 2 grams twice daily on Day 1 followed by 1 gram twice daily on Day 2, or placebo on Days 1 and 2.

The mean duration of cold sore episodes was about 1 day shorter in treated subjects as compared with placebo. The 2-day regimen did not offer additional benefit over the 1-day regimen.

No significant difference was observed between subjects receiving VALTREX or placebo in the prevention of progression of cold sore lesions beyond the papular stage.

14.2 Genital Herpes Infections

Initial Episode

Six hundred forty-three immunocompetent adults with first-episode genital herpes who presented within 72 hours of symptom onset were randomized in a double-blind trial to receive 10 days of VALTREX 1 gram twice daily (n = 323) or oral acyclovir 200 mg 5 times a day (n = 320). For both treatment groups the median time to lesion healing was 9 days, the median time to cessation of pain was 5 days, and the median time to cessation of viral shedding was 3 days.

Recurrent Episodes

Three double-blind trials (2 of them placebo-controlled) in immunocompetent adults with recurrent genital herpes were conducted. Subjects self-initiated therapy within 24 hours of the first sign or symptom of a recurrent genital herpes episode.

In 1 trial, subjects were randomized to receive 5 days of treatment with either VALTREX 500 mg twice daily (n = 360) or placebo (n = 259). The median time to lesion healing was 4 days in the group receiving VALTREX 500 mg versus 6 days in the placebo group, and the median time to cessation of viral shedding in subjects with at least 1 positive culture (42% of the overall trial population) was 2 days in the group receiving VALTREX 500 mg versus 4 days in the placebo group. The median time to cessation of pain was 3 days in the group receiving VALTREX 500 mg versus 4 days in the placebo group. Results supporting efficacy were replicated in a second trial.

In a third trial, subjects were randomized to receive VALTREX 500 mg twice daily for 5 days (n = 398) or VALTREX 500 mg twice daily for 3 days (and matching placebo twice daily for 2 additional days) (n = 402). The median time to lesion healing was about 4½ days in both treatment groups. The median time to cessation of pain was about 3 days in both treatment groups.

Suppressive Therapy

Two clinical trials were conducted, one in immunocompetent adults and one in HIV-1 –infected adults.

A double‑blind, 12‑month, placebo‑ and active‑controlled trial enrolled immunocompetent adults with a history of 6 or more recurrences per year. Outcomes for the overall trial population are shown in Table 8.

Table 8. Recurrence Rates in Immunocompetent Adults at 6 and 12 Months
Outcome | 6 Months |  |  | 12 Months
Outcome | VALTREX; 1 gram; Once Daily; (n = 269) | Oral Acyclovir; 400 mg; Twice Daily; (n = 267) | Placebo; (n = 134) | VALTREX; 1 gram; Once Daily; (n = 269) | Oral Acyclovir; 400 mg; Twice Daily; (n = 267) | Placebo; (n = 134)
Recurrence free | 55% | 54% | 7% | 34% | 34% | 4%
Recurrences | 35% | 36% | 83% | 46% | 46% | 85%
Unknowna | 10% | 10% | 10% | 19% | 19% | 10%
a Includes lost to follow-up, discontinuations due to adverse events, and consent withdrawn.

Subjects with 9 or fewer recurrences per year showed comparable results with VALTREX 500 mg once daily.

In a second trial, 293 HIV‑1 –infected adults on stable antiretroviral therapy with a history of 4 or more recurrences of ano‑genital herpes per year were randomized to receive either VALTREX 500 mg twice daily (n = 194) or matching placebo (n = 99) for 6 months. The median duration of recurrent genital herpes in enrolled subjects was 8 years, and the median number of recurrences in the year prior to enrollment was 5. Overall, the median pretrial HIV‑1 RNA was 2.6 log10 copies/mL. Among subjects who received VALTREX, the pretrial median CD4+ cell count was 336 cells/mm^3; 11% had less than 100 cells/mm^3, 16% had 100 to 199 cells/mm^3, 42% had 200 to 499 cells/mm^3, and 31% had greater than or equal to 500 cells/mm^3. Outcomes for the overall trial population are shown in Table 9.

Table 9. Recurrence Rates in HIV-1–Infected Adults at 6 Months
Outcome | VALTREX; 500 mg Twice Daily; (n = 194) | Placebo; (n = 99)
Recurrence free | 65% | 26%
Recurrences | 17% | 57%
Unknowna | 18% | 17%
a Includes lost to follow-up, discontinuations due to adverse events, and consent withdrawn.

Reduction of Transmission of Genital Herpes

A double‑blind, placebo‑controlled trial to assess transmission of genital herpes was conducted in 1,484 monogamous, heterosexual, immunocompetent adult couples. The couples were discordant for HSV‑2 infection. The source partner had a history of 9 or fewer genital herpes episodes per year. Both partners were counseled on safer sex practices and were advised to use condoms throughout the trial period. Source partners were randomized to treatment with either VALTREX 500 mg once daily or placebo once daily for 8 months. The primary efficacy endpoint was symptomatic acquisition of HSV‑2 in susceptible partners. Overall HSV‑2 acquisition was defined as symptomatic HSV‑2 acquisition and/or HSV‑2 seroconversion in susceptible partners. The efficacy results are summarized in Table 10.

Table 10. Percentage of Susceptible Partners Who Acquired HSV-2 Defined by the Primary and Selected Secondary Endpoints
Endpoint | VALTREXa; (n = 743) | Placebo; (n = 741)
Symptomatic HSV‑2 acquisition | 4 (0.5%) | 16 (2.2%)
HSV‑2 seroconversion | 12 (1.6%) | 24 (3.2%)
Overall HSV‑2 acquisition | 14 (1.9%) | 27 (3.6%)
a Results show reductions in risk of 75% (symptomatic HSV‑2 acquisition), 50% (HSV‑2 seroconversion), and 48% (overall HSV‑2 acquisition) with VALTREX versus placebo. Individual results may vary based on consistency of safer sex practices.

14.3 Herpes Zoster

Two randomized, double‑blind clinical trials in immunocompetent adults with localized herpes zoster were conducted. VALTREX was compared with placebo in subjects aged less than 50 years and with oral acyclovir in subjects aged greater than 50 years. All subjects were treated within 72 hours of appearance of zoster rash. In subjects aged less than 50 years, the median time to cessation of new lesion formation was 2 days for those treated with VALTREX compared with 3 days for those treated with placebo. In subjects aged greater than 50 years, the median time to cessation of new lesions was 3 days in subjects treated with either VALTREX or oral acyclovir. In subjects aged less than 50 years, no difference was found with respect to the duration of pain after healing (post‑herpetic neuralgia) between the recipients of VALTREX and placebo. In subjects aged greater than 50 years, among the 83% who reported pain after healing (post‑herpetic neuralgia), the median duration of pain after healing (95% CI) in days was: 40 (31, 51), 43 (36, 55), and 59 (41, 77) for 7‑day VALTREX, 14‑day VALTREX, and 7‑day oral acyclovir, respectively.

14.4 Chickenpox

The use of VALTREX for treatment of chickenpox in pediatric subjects aged 2 to less than 18 years is based on single‑dose pharmacokinetic and multiple‑dose safety data from an open‑label trial with valacyclovir and supported by safety and extrapolated efficacy data from 3 randomized, double‑blind, placebo‑controlled trials evaluating oral acyclovir in pediatric subjects.

The single‑dose pharmacokinetic and multiple‑dose safety trial enrolled 27 pediatric subjects aged 1 to less than 12 years with clinically suspected VZV infection. Each subject was dosed with valacyclovir oral suspension, 20 mg/kg 3 times daily for 5 days. Acyclovir systemic exposures in pediatric subjects following valacyclovir oral suspension were compared with historical acyclovir systemic exposures in immunocompetent adults receiving the solid oral dosage form of valacyclovir or acyclovir for the treatment of herpes zoster. The mean projected daily acyclovir exposures in pediatric subjects across all age‑groups (1 to less than 12 years) were lower (Cmax: ↓13%, AUC: ↓30%) than the mean daily historical exposures in adults receiving valacyclovir 1 gram 3 times daily, but were higher (daily AUC: ↑50%) than the mean daily historical exposures in adults receiving acyclovir 800 mg 5 times daily. The projected daily exposures in pediatric subjects were greater (daily AUC approximately 100% greater) than the exposures seen in immunocompetent pediatric subjects receiving acyclovir 20 mg/kg 4 times daily for the treatment of chickenpox. Based on the pharmacokinetic and safety data from this trial and the safety and extrapolated efficacy data from the acyclovir trials, oral valacyclovir 20 mg/kg 3 times a day for 5 days (not to exceed 1 gram 3 times daily) is recommended for the treatment of chickenpox in pediatric patients aged 2 to less than 18 years. Because the efficacy and safety of acyclovir for the treatment of chickenpox in children aged less than 2 years have not been established, efficacy data cannot be extrapolated to support valacyclovir treatment in children aged less than 2 years with chickenpox. Valacyclovir is also not recommended for the treatment of herpes zoster in children because safety data up to 7 days’ duration are not available [see Use in Specific Populations (8.4)] .

16 HOW SUPPLIED/STORAGE AND HANDLING

VALTREX tablets (blue, film-coated, capsule-shaped tablets, with a partial scorebar on both sides, printed with “VALTREX 1 gram”) containing 1.112 grams of valacyclovir hydrochloride equivalent to 1 gram of valacyclovir.

NDC: 70518-2039-00

NDC: 70518-2039-01

NDC: 70518-2039-02

PACKAGING: 10 in 1 BOTTLE PLASTIC

PACKAGING: 14 in 1 BOTTLE PLASTIC

PACKAGING: 5 in 1 BOTTLE PLASTIC

Storage:

Store at 15°C to 25°C (59°F to 77°F). Dispense in a well-closed container as defined in the USP.

Repackaged and Distributed By:

Remedy Repack, Inc.

625 Kolter Dr. Suite #4 Indiana, PA 1-724-465-8762

17 PATIENT COUNSELING INFORMATION

Advise the patient to read the FDA-approved patient labeling (Patient Information).

Severe Cutaneous Adverse Reactions

Inform patients that severe skin reactions including acute generalized exanthematous pustulosis (AGEP), drug reaction with eosinophilia and systemic symptoms (DRESS), toxic epidermal necrolysis (TEN), Stevens‑Johnson syndrome (SJS), and erythema multiforme (EM) have been reported with valacyclovir. Advise patients to immediately contact their healthcare provider if they develop a rash. Instruct patients to immediately stop taking VALTREX and seek medical attention if a painful rash with mucosal involvement develops [see Contraindications (4), Warnings and Precautions (5.4), Adverse Reactions (6.3)] .

Importance of Adequate Hydration

Patients should be advised to maintain adequate hydration.

Missed Dose

Instruct patients that if they miss a dose of VALTREX, to take it as soon as they remember. Advise patients not to double their next dose or take more than the prescribed dose.

Cold Sores (Herpes Labialis)

Patients should be advised to initiate treatment at the earliest symptom of a cold sore (e.g., tingling, itching, or burning). There are no data on the effectiveness of treatment initiated after the development of clinical signs of a cold sore (e.g., papule, vesicle, or ulcer). Patients should be instructed that treatment for cold sores should not exceed 1 day (2 doses) and that their doses should be taken about 12 hours apart. Patients should be informed that VALTREX is not a cure for cold sores.

Genital Herpes

Patients should be informed that VALTREX is not a cure for genital herpes. Because genital herpes is a sexually transmitted disease, patients should avoid contact with lesions or intercourse when lesions and/or symptoms are present to avoid infecting partners. Genital herpes is frequently transmitted in the absence of symptoms through asymptomatic viral shedding. Therefore, patients should be counseled to use safer sex practices in combination with suppressive therapy with VALTREX. Sex partners of infected persons should be advised that they might be infected even if they have no symptoms. Type‑specific serologic testing of asymptomatic partners of persons with genital herpes can determine whether risk for HSV‑2 acquisition exists.

VALTREX has not been shown to reduce transmission of sexually transmitted infections other than HSV‑2.

If medical management of a genital herpes recurrence is indicated, patients should be advised to initiate therapy at the first sign or symptom of an episode.

There are no data on the effectiveness of treatment initiated more than 72 hours after the onset of signs and symptoms of a first episode of genital herpes or more than 24 hours after the onset of signs and symptoms of a recurrent episode.

There are no data on the safety or effectiveness of chronic suppressive therapy of more than 1 year’s duration in otherwise healthy patients. There are no data on the safety or effectiveness of chronic suppressive therapy of more than 6 months’ duration in HIV-1−infected patients.

Herpes Zoster

There are no data on treatment initiated more than 72 hours after onset of the zoster rash. Patients should be advised to initiate treatment as soon as possible after a diagnosis of herpes zoster.

Chickenpox

Patients should be advised to initiate treatment at the earliest sign or symptom of chickenpox.

Trademarks are owned by or licensed to the GSK group of companies.

Repackaged By / Distributed By: RemedyRepack Inc.

625 Kolter Drive, Indiana, PA 15701

(724) 465-8762

PATIENT INFORMATION

VALTREX (VAL-trex)

(valacyclovir)

tablets

What is VALTREX?

VALTREX is a prescription medicine used in adults:

- to treat cold sores (herpes labialis).
- to treat or control genital herpes outbreaks in adults with normal immune systems.
- to control genital herpes outbreaks in adults with human immunodeficiency virus-1 (HIV-1).
- with safer sex practices to lower the chance of spreading genital herpes to others, in adults with normal immune systems. Even with safer sex practices, it is still possible to spread genital herpes.
  - Do not have sexual contact with your partner when you have any symptom or outbreak of genital herpes.
  - Use a condom made of latex or polyurethane whenever you have sexual contact.
  - Ask your healthcare provider for more information about safer sex practices.
- to treat shingles (herpes zoster) in adults with normal immune systems.

VALTREX is used in children to treat:

- cold sores in children 12 years of age and older.
- chickenpox in children with normal immune systems 2 years of age to less than 18 years of age.

VALTREX does not curecold sores, chickenpox, shingles, or genital herpes.

- It is not known if VALTREX is safe and effective in people with weakened immune systems, other than for control of outbreaks of genital herpes in people with HIV-1.
- It is not known if VALTREX is safe and effective in people 18 years of age and older with chickenpox.
- It is not known if VALTREX is safe and effective in children:
  - less than 12 years of age with cold sores
  - less than 2 years of age with chickenpox
  - less than 18 years of age with genital herpes or shingles

Do not take VALTREXif you are allergic to valacyclovir, acyclovir, or any of the ingredients in VALTREX. See the end of this leaflet for a complete list of ingredients in VALTREX.

Before you take VALTREX, tell your healthcare provider about all of your medical conditions, including if you:

- have had severe skin reactionswith VALTREX or acyclovir.
- have had a bone marrow transplant or kidney transplant, or if you have advanced HIV-1 infection or acquired immune deficiency syndrome (AIDS).
- have kidney problems, including if you receive dialysis.
- are pregnant or plan to become pregnant. It is not known if VALTREX will harm your unborn baby. You and your healthcare provider will decide if you will take VALTREX if you are pregnant.
- are breastfeeding or plan to breastfeed. VALTREX may pass into your breastmilk. Talk with your healthcare provider about the best way to feed your child if you take VALTREX.

Tell your healthcare provider about all the medicines you take,including prescription and over-the-counter medicines, vitamins, and herbal supplements.

How should I take VALTREX?

- Take VALTREX exactly as your healthcare provider tells you to take it.
- Your dose of VALTREX and length of treatment will depend on the type of infection that you have and any other medical problems that you have.
- Do not stop VALTREX or change your treatment without talking to your healthcare provider.
- Take VALTREX with or without food.
- Tell your healthcare provider if your child cannot swallow VALTREX tablets. Your healthcare provider can prescribe VALTREX as an oral suspension for your child.
- If you are taking VALTREX to treat outbreaks of cold sores, chickenpox, shingles, or genital herpes, take VALTREX as soon as you have the first symptoms of infection such as tingling, itching, or burning, or when the sore appears.
- It is important for you to stay well hydrated during treatment with VALTREX. Be sure to drink plenty of fluids during this time.
- If you miss a dose of VALTREX, take it as soon as you remember. If it is almost time for your next dose, do not take the missed dose. Take the next dose at your regular time. Do not take 2 doses at the same time or take more VALTREX than prescribed.
- If you take too much VALTREX, call your healthcare provider or go to the nearest hospital emergency room right away.

What are the possible side effects of VALTREX?

VALTREX can cause serious side effects including:

- Thrombotic Thrombocytopenic Purpura (TTP) and Hemolytic Uremic Syndrome (HUS).TTP and HUS have happened in people with weakened immune systems taking VALTREX and have led to death. TTP and HUS are disorders that can cause small blood clots to form throughout the body and decrease blood flow to body organs such as the brain, heart, and kidneys. Your healthcare provider will stop treatment with VALTREX if you have signs or symptoms of TTP and HUS.
- kidney failure.
- nervous system problems.Tell your healthcare provider right away if you get any of these signs or symptoms of nervous system problems during treatment with VALTREX:

- aggressive behavior
- unsteady movement
- shaky movements
- confusion

- speech problems
- hallucinations (seeing or hearing things that are really not there)
- seizures
- coma

- severe skin reactions.Severe skin reactions have happened in people treated with VALTREX. Tell your healthcare provider right away if you develop a rash during treatment with VALTREX. Stop taking VALTREX immediately and get medical help right away if you develop a painful rash with any of the following symptoms:blisters or sores in the mouth, or blisters or peeling of the skin.

Elderly people are more likely to get certain side effects. Talk to your healthcare provider if this is a concern for you.

The most common side effects of VALTREX in adults include:

- headache
- nausea

- stomach (abdominal) pain

The most common side effect of VALTREX in children less than 18 years of age is headache.

These are not all the possible side effects of VALTREX.

Call your doctor for medical advice about side effects. You may report side effects to FDA at 1‑800‑FDA‑1088.

How should I store VALTREX?

- Store VALTREX tablets at 59°F to 77°F (15°C to 25°C).
- Store VALTREX suspension between 36°F to 46°F (2°C to 8°C) in a refrigerator. Throw away (discard) any remaining VALTREX suspension after 28 days.
- Shake VALTREX suspension bottle well before using.
- Keep VALTREX in a tightly closed container.

Keep VALTREX and all medicines out of the reach of children.

General information about the safe and effective use of VALTREX.

Medicines are sometimes prescribed for purposes other than those listed in a Patient Information leaflet. Do not use VALTREX for a condition for which it was not prescribed. Do not give VALTREX to other people, even if they have the same symptoms that you have. It may harm them. You can ask your healthcare provider or pharmacist for information about VALTREX that is written for health professionals.

What are the ingredients in VALTREX?

Active ingredient: valacyclovir hydrochloride

Inactive ingredients:carnauba wax, colloidal silicon dioxide, crospovidone, FD&C Blue No. 2 Lake, hypromellose, magnesium stearate, microcrystalline cellulose, polyethylene glycol, polysorbate 80, povidone, and titanium dioxide.

Trademarks are owned by or licensed to the GSK group of companies.

©2025 GSK group of companies or its licensor.

Repackaged and Distributed By:

Remedy Repack, Inc.

625 Kolter Dr. Suite #4 Indiana, PA 1-724-465-8762

This Patient Information has been approved by the U.S. Food and Drug Administration.

Revised: November 2025

PACKAGE LABEL

DRUG: VALTREX

GENERIC: valacyclovir hydrochloride

DOSAGE: TABLET, FILM COATED

ADMINSTRATION: ORAL

NDC: 70518-2039-0

NDC: 70518-2039-1

NDC: 70518-2039-2

COLOR: blue

SHAPE: OVAL

SCORE: Two even pieces

SIZE: 23 mm

IMPRINT: VALTREX;1;gram

PACKAGING: 10 in 1 BOTTLE PLASTIC

PACKAGING: 14 in 1 BOTTLE PLASTIC

PACKAGING: 5 in 1 BOTTLE PLASTIC

ACTIVE INGREDIENT(S):

- VALACYCLOVIR HYDROCHLORIDE 1g in 1

INACTIVE INGREDIENT(S):

- CARNAUBA WAX
- SILICON DIOXIDE
- CROSPOVIDONE (120 .MU.M)
- FD&C BLUE NO. 2
- HYPROMELLOSE, UNSPECIFIED
- MAGNESIUM STEARATE
- MICROCRYSTALLINE CELLULOSE
- POLYETHYLENE GLYCOL, UNSPECIFIED
- POLYSORBATE 80
- POVIDONE, UNSPECIFIED
- TITANIUM DIOXIDE